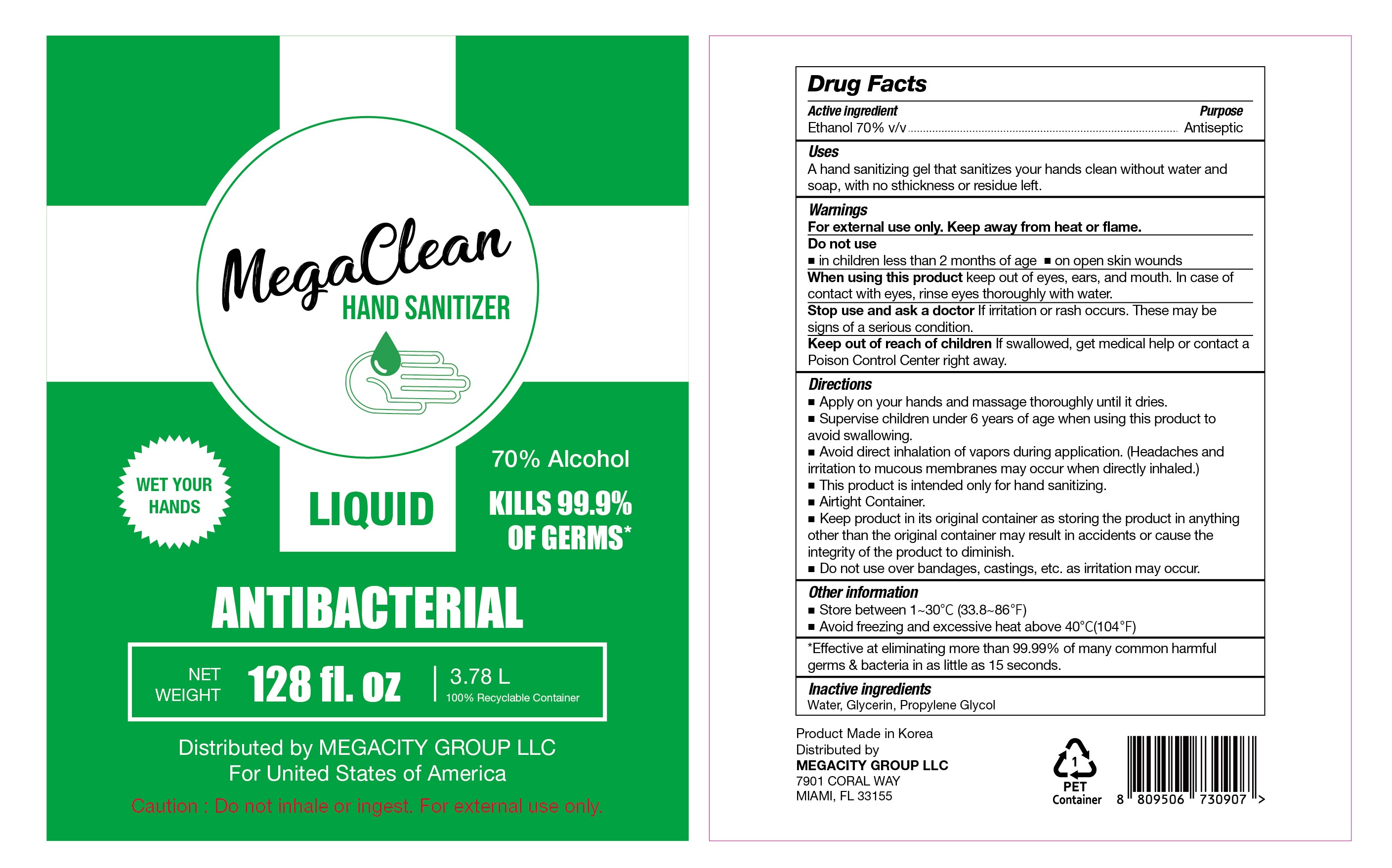 DRUG LABEL: MegaClean HAND SANITIZER Liquid
NDC: 77799-002 | Form: LIQUID
Manufacturer: MEGACITY GROUP LLC
Category: otc | Type: HUMAN OTC DRUG LABEL
Date: 20200531

ACTIVE INGREDIENTS: ALCOHOL 2646 mL/3780 mL
INACTIVE INGREDIENTS: GLYCERIN; WATER; PROPYLENE GLYCOL

MegaClean HAND SANITIZER LIQUID 1 Gallon Liquid type